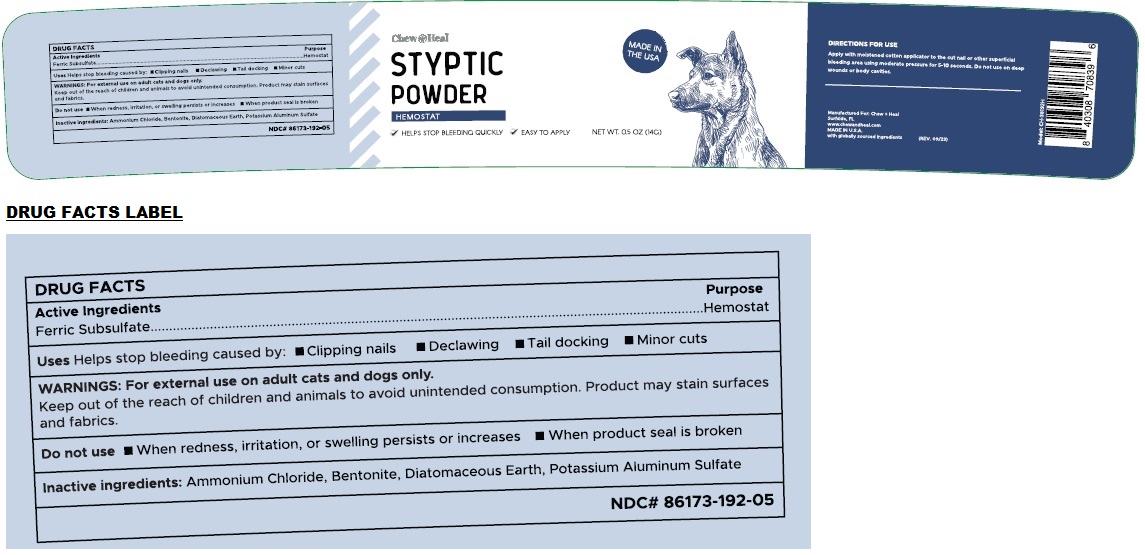 DRUG LABEL: Styptic Powder
NDC: 86173-192 | Form: POWDER
Manufacturer: Click Industries LLC
Category: animal | Type: OTC ANIMAL DRUG LABEL
Date: 20240418

ACTIVE INGREDIENTS: FERRIC SUBSULFATE 35 g/100 g
INACTIVE INGREDIENTS: AMMONIUM CHLORIDE; BENTONITE; DIATOMACEOUS EARTH; POTASSIUM SULFATE

STYPTIC POWDER

Active Ingredients

Ferric Subsulfate

Purpose

Hemostat

Uses

Helps stop bleeding caused by: • Clipping nails • Declawing • Tail docking • Minor cuts

WARNINGS:

For external use on adult cats and dogs only.
Keep out of the reach of children and animals to avoid unintended consumption. Product may stain surfaces and fabrics.

Do not use • When redness, irritation, or swelling persists or increases • When product seal is broken

Inactive ingredients:

Ammonium Chloride, Bentonite, Diatomaceous Earth, Potassium Aluminum Sulfate

DIRECTIONS FOR USE

Apply with moistened cotton applicator to the cut nail or other superficial bleeding area using moderate pressure for 5-10 seconds. Do not use on deep wounds or body cavities.

√ HELPS STOP BLEEDING QUICKLY √ EASY TO APPLY

Manufactured For: Chew + Heal
Surfside, FL
www.chewandheal.com
MADE IN U.S.A.
with globally sourced ingredients